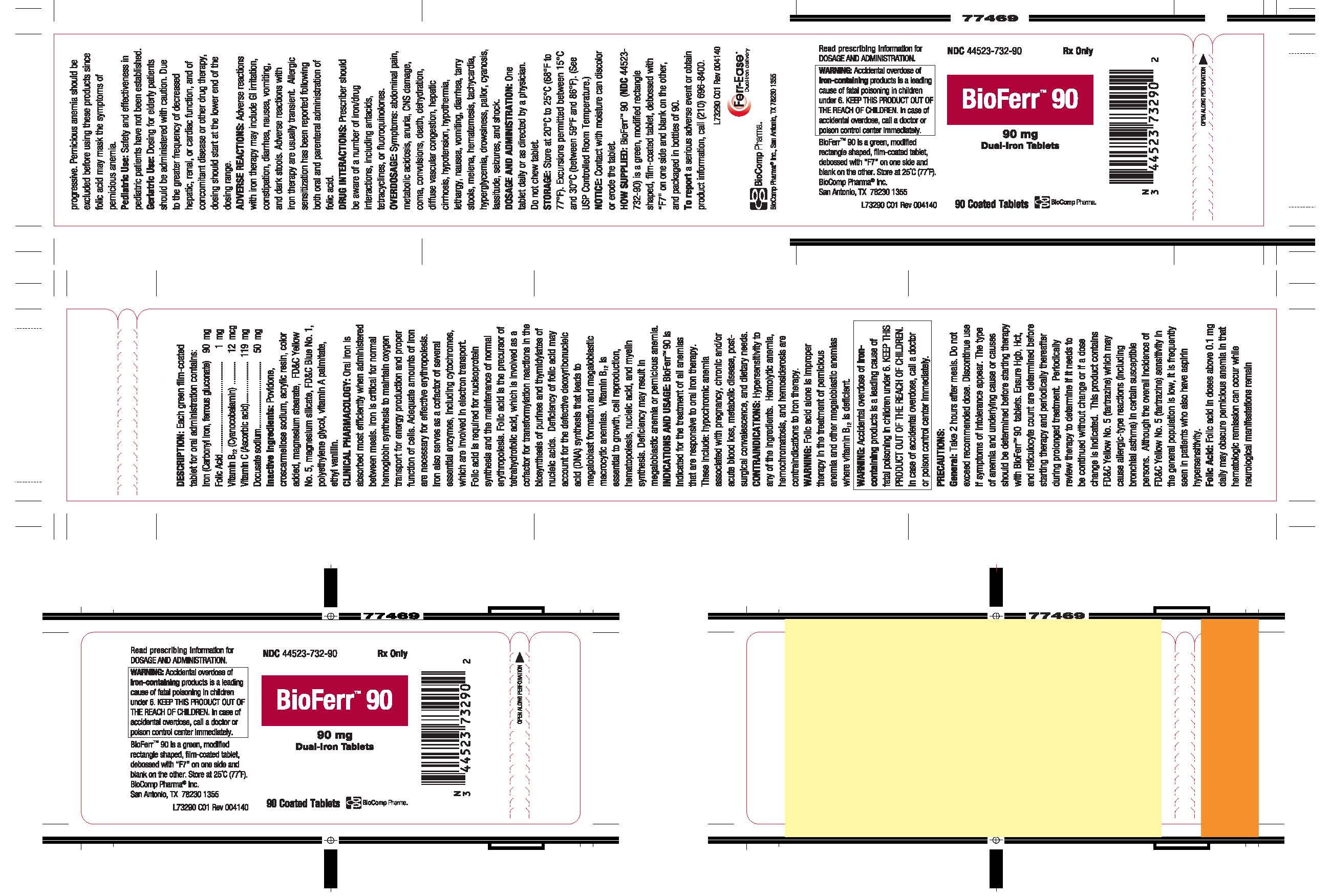 DRUG LABEL: BioFerr 90
NDC: 44523-732 | Form: TABLET, FILM COATED
Manufacturer: Biocomp Pharma, Inc.
Category: prescription | Type: HUMAN PRESCRIPTION DRUG LABEL
Date: 20140618

ACTIVE INGREDIENTS: ASCORBIC ACID 138 mg/1 1; IRON PENTACARBONYL 88.5 mg/1 1; DOCUSATE SODIUM 55 mg/1 1; FERROUS GLUCONATE 13.2 mg/1 1; FOLIC ACID 1.4 mg/1 1; CYANOCOBALAMIN 16.8 ug/1 1
INACTIVE INGREDIENTS: POVIDONES; CROSCARMELLOSE SODIUM; DIMETHYLAMINOETHYL METHACRYLATE - BUTYL METHACRYLATE - METHYL METHACRYLATE COPOLYMER; TITANIUM DIOXIDE; MAGNESIUM STEARATE; FD&C YELLOW NO. 5; MAGNESIUM SILICATE; FD&C BLUE NO. 1; POLYETHYLENE GLYCOLS; VITAMIN A PALMITATE; ETHYL VANILLIN

BioFerr™ 90

BOXED WARNING

Warning: Accidental overdose of iron-containing products is a leading cause of fatal poisoning in children under 6. KEEP THIS PRODUCT OUT OF THE REACH OF CHILDREN. In case of accidental overdose, call a doctor or poison control center immediately.

DESCRIPTION:

Each green film-coated tablet for oral administration contains:

ACTIVE INGREDIENT

Iron (Carbonyl iron, ferrous gluconate) | 90 | mg
Folic Acid | 1 | mg
Vitamin B12 (Cyanocobalamin) | 12 | mcg
Vitamin C (Ascorbic acid) | 119 | mg
Docusate sodium | 50 | mg

Inactive Ingredients:

Povidone, croscarmellose sodium, acrylic resin, color added, magnesium stearate, FD&C Yellow No. 5, magnesium silicate, FD&C Blue No. 1, polyethylene glycol, vitamin A palmitate, ethyl vanillin.

CLINICAL PHARMACOLOGY:

Oral iron is absorbed most efficiently when administered between meals. Iron is critical for normal hemoglobin synthesis to maintain oxygen transport for energy production and proper function of cells. Adequate amounts of iron are necessary for effective erythropolesis. Iron also serves as a cofactor of several essential enzymes, Including cytochromes, which are involved in electron transport. Folic acid is required for nucleoprotein synthesis and the maintenance of normal erytropolesis. Folic acid is the precursor of tetrahydrofolic acid, which is involved as a cofactor for transformylation reactions In the biosynthesis of purines and thymidylates of nucleic acids. Deficiency of folic acid may account for the defective deoxyribonucleic acid (DNA) synthesis that leads to megaloblast formation and megaloblastic macrocytic anemias. Vitamin B12 is essential to growth, cell reproduction, hematopolesis, nucleic acid, and myelin synthesis. Deficiency may result in megaloblastic anemia or pernicious anemia.

INDICATIONS AND USAGE:

BioFerr™ 90 is indicated for the treatment of all anemias that are responsive to oral iron therapy. These include: hypochromic anemia associated with pregnancy, chronic and/or acute blood loss, metabolic disease, post-surgical convalescence, and dietary needs.

CONTRAINDICATIONS:

Hypersensitivity to any of the ingredients. Hemolytic anemia, hemochromatosis, and hemosiderosis are contraindications to iron therapy.

WARNING:

Folic acid alone is improper therapy in the treatment of pernicious anemia and other megaloblastic anemia where vitamin B12 is deficient.

PRECAUTIONS:

General:

Take 2 hours after meals. Do not exceed recommended dose. Discontinue use if symptoms of intolerance appear. The type of anemia and underlying cause or causes should be determined before starting therapy with BioFerr™ 90 tablets. Ensure Hgb, Hct, and reticulocyte count are determined before starting therapy to determine if it needs to be continued without change or if a dose change is indicated. This product contains FD&C Yellow No. 5 (tartrazine) which may cause allergic-type reactions (including bronchial asthma) in certain susceptible persons. Although the overall incidence of FD&C Yellow No. 5 (tartrazine) sensitivity in the general population is low, it is frequently seen in patients who also have aspirin hypersensitivity.

Folic Acid:

Folic acid in doses above 0.1 mg daily may obscure pernicious anemia in that hematologic remission can occur while neurological manifestations remain progressive. Pernicious anemia should be excluded before using these products since folic acid may mask the symptoms of pernicious anemia.

Pediatric Use:

Safety and effectiveness in pediatric patients have not been established.

Geriatric Use:

Dosing for elderly patients should be administered with caution. Due to the greater frequency of decreased hepatic, renal, or cardiac function, and of concomitant disease or other drug therapy, dosing should start at the lower end of the dosing range.

ADVERSE REACTIONS:

Adverse reactions with iron therapy may include GI irritation, constipation, diarrhea, nausea, vomiting, and dark stools. Adverse reactions with iron therapy are usually transient. Allergic sensitization has been reported following both oral and parenteral administration of folic acid.

DRUG INTERACTIONS:

Prescriber should be aware of a number of iron/drug interactions, including antacids, tetracyclines, or fluoroquinolones.

OVERDOSAGE:

Symptoms: abdominal pain, metabolic acidosis, anuria, CNS damage, coma, convulsions, death, dehydration, diffuse vascular congestion, hepatic cirrhosis, hypotension, hypothermia, lethargy, nausea, vomiting, diarrhea, tarry stools, melena, hematernesis, tachycardia, hyperglycemia, drowsiness, pallor, cyanosis, lassitude, seizures, and shock

DOSAGE AND ADMINISTRATION

One tablet daily or as directed by a physician.
Do not chew tablet.

STORAGE:

Store at 20°C to 25°C (68°F to 77°F). Excursions permitted between 15°C and 30°C (between 59°F and 86°F). (See USP Controlled Room Temperature.)℃

NOTICE:

Contact with moisture can discolor or erode the tablet.

HOW SUPPLIED:

BioFerr™ 90 (NDC 44523-732-90) is a green, modified rectangle shaped, film-coated tablet, debossed with “F7” on one side and blank on the other, and packaged in bottles of 90.

To report a serious adverse event or obtain product information, call (210) 696-8400.

L73290 C01 Rev 004140
BioComp Pharma® Inc., San Antonio, TX 78230 1355

PACKAGE LABEL

BioFerr™ 90
90 mg Dual-Iron Tablets
NDC 44523-732-90